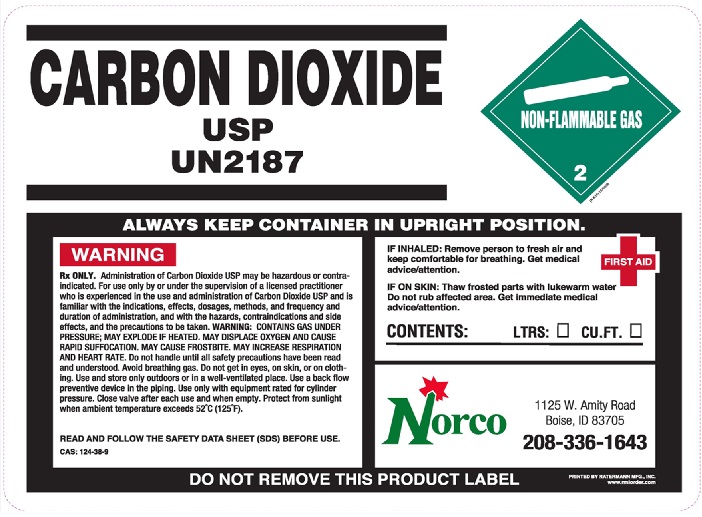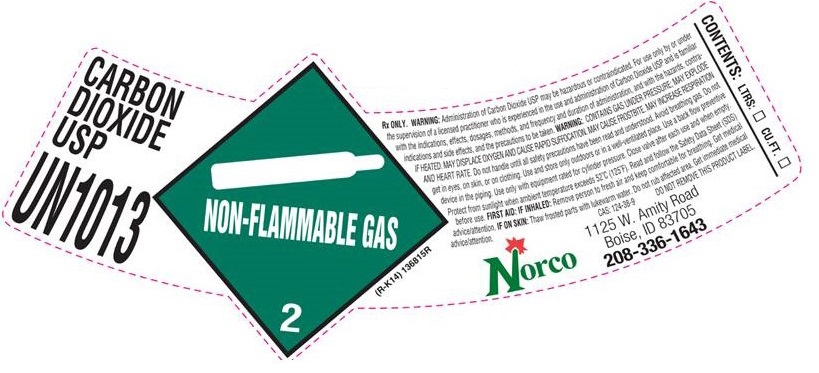 DRUG LABEL: CARBON DIOXIDE
NDC: 42602-006 | Form: GAS
Manufacturer: Norco, Inc
Category: prescription | Type: HUMAN PRESCRIPTION DRUG LABEL
Date: 20251215

ACTIVE INGREDIENTS: CARBON DIOXIDE 99 L/100 L

CARBON DIOXIDE USP HP LABEL

CARBON DIOXIDE USP

UN1013 (R-K14 136815R)

NON-FLAMMABLE GAS 2

Rx ONLY. WARNING:Administration of Carbon Dioxide USP may be hazardous or contraindicated. For use only by or under
the supervision of a licensed practitioner who is experienced in the use and administration of Carbon Dioxide USP and is familiar
with the indications, effects, dosages, methods, and frequency and duration of administration, and with the hazards, contra-
indications and side effects, and the precautions to be taken. WARNING:CONTAINS GAS UNDER PRESSURE; MAY EXPLODE
IF HEATED. MAY DISPLACE OXYGEN AND CAUSE RAPID SUFFOCATION. MAY CAUSE FROSTBITE. MAY INCREASE RESPIRATION
AND HEART RATE. Do not handle until all safety precautions have been read and understood. Avoid breathing gas. Do not
get in eyes, on skin, or on clothing. Use and store only outdoors or in a well-ventilated place. Use a back flow preventive
device in the piping. Use only with equipment rated for cylinder pressure. Close valve after each use and when empty.
Protect from sunlight. when ambient temperature exceeds 52 C (125 F). Read and follow the Safety Data Sheet (SDS)
Before use. FIRST AID: IF INHALED: Remove person to fresh air and keep comfortable for breathing. Get medical
advice/attention. IF ON SKIN:Thaw frosted parts with lukewarm water. Do not rub affected area. Get immediate medical
advice/attention. CAS 124-38-9 DO NOT REMOVE THIS PRODUCT LABEL

Norco

1125 W. Amity Road
Boise, ID 83705
208-336-1643

CONTENTS: LTRS: __ CU.FT. __

res

≈≈≈≈≈≈≈≈≈≈≈≈≈≈≈≈≈≈≈≈≈≈≈≈≈≈≈≈≈≈≈≈≈≈≈≈≈≈≈≈≈≈≈≈≈≈≈≈≈≈≈≈≈≈≈≈≈≈≈≈≈≈≈≈≈≈≈≈≈≈≈≈≈≈≈≈≈≈≈

CARBON DIOXIDE USP LIQUID LABEL

CARBON DIOXIDE USP

UN2187

NON-FLAMMABLE GAS 2

(R-K14)

ALWAYS KEEP CONTAINER IN UPRIGHT POSITION.

WARNING

Rx ONLY.Administration of Carbon Dioxide USP may be hazardous or contra-
indicated. For use only by or under the supervision of a licensed practitioner
who is experienced in the use and administration of Carbon Dioxide USP and is
familiar with the indications, effects, dosages, methods, and frequency and
duration of administration, and with the hazards, contraindications and side
effects, and the precautions to be taken. WARNING:CONTAINS GAS UNDER
PRESSURE; MAY EXPLODE IF HEATED. MAY DISPLACE OXYGEN AND CAUSE
RAPID SUFFOCATION. MAY CAUSE FROSTBITE. MAY INCREASE RESPIRATION
AND HEART RATE. Do not handle until all safety precautions have been read
and understood. Avoid breathing gas. Do not get in eyes, on skin, or on cloth-
ing. Use and store only outdoors or in a well-ventilated place. Use a back flow
preventive device in the piping. Use only with equipment rated for cylinder
pressure. Close valve after each use and when empty. Protect from sunlight
when ambient temperature exceeds 52 C (125 F).

READ AND FOLLOW THE SAFETY DATE SHEET (SDS) BEFORE USE.

CAS 124-38-9

FIRST AID
IF INHALED:Remove person to fresh air and
keep comfortable for breathing. Get medical
advice/attention.

IF ON SKIN:Thaw frosted parts with lukewarm water.
Do not rub affected area. Get immediate medical
advice/attention.

CONTENTS: LTRS: __ CU.FT. __

Norco
1125 W. Amity Road
Boise, ID 83705
208-336-1643

DO NOT REMOVE THIS PRODUCT LABEL

res